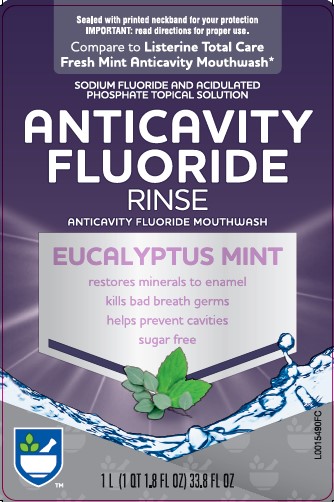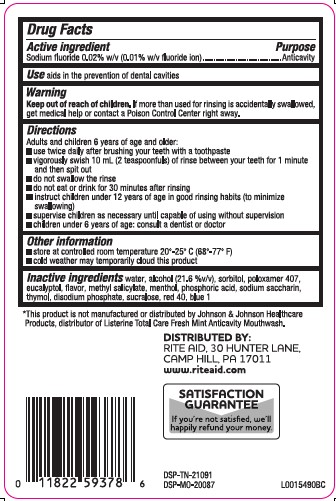 DRUG LABEL: Anticavity
NDC: 11822-5927 | Form: MOUTHWASH
Manufacturer: Rite Aid Corporation
Category: otc | Type: HUMAN OTC DRUG LABEL
Date: 20260130

ACTIVE INGREDIENTS: SODIUM FLUORIDE 0.1 mg/1 mL
INACTIVE INGREDIENTS: WATER; ALCOHOL; SORBITOL; POLOXAMER 407; EUCALYPTOL; METHYL SALICYLATE; MENTHOL; PHOSPHORAMIDIC ACID; SACCHARIN SODIUM; THYMOL; SODIUM PHOSPHATE, DIBASIC, ANHYDROUS; SUCRALOSE; FD&C RED NO. 40; FD&C BLUE NO. 1

Rite Aid 163.005/163AF-AG
Anticavity Mouthwash

Active ingredient

Sodium fluoride 0.0221% (0.01% w/v fluoride ion)

Purpose

Anticavity

Use

aids in the prevention of dental cavities

Warnings

for this product

Keep out of reach of children.

If more than used for rinsing is accidentally swallowed, get medical help or contact a Poison Control Center right away.

Directions

Adults and Children 6 years of age and older:

- use twice daily after brushing your teeth with a toothpaste
- vigorously swish 10 mL (2 teaspoonfuls) of rinse between your teeth for 1 minute and then spit out
- do not swallow the rinse
- do not eat or drink for 30 minutes after rinsing
- instruct children uder 12 years of age in good rinsing habits (to minimize swallowing)
- supervise children as necessary until capable of using without supervision
- children under 6 years of age: consult a dentist or doctor

Other information

- store at controlled room temperature 20°-25° C to (68° - 77°F)
- cold weather may temporarily cloud this product

Inactive ingredients

water, alcohol (21.6%), sorbitol, poloxamer 407, eucalyptol, flavor, methyl salicylate, menthol, phosphoric acid, sodium saccharin, thymol, disodium posphate, sucralose, red 40, blue 1

Disclaimer

*This product is not manufactured or distributed by Johnson & Johnson Healthcare Products, distributor of Listerine Total Care Fresh Mint Anticavity Mouthwash.

Adverse reaction section

DISTRIBUTED BY:

RITE AID, 30 HUNTER LANE

CAMP HILL, PA 17011

www.riteaid.com

SATISFACTION GUARANTEE

If you're not satisfied, we'll happily refund your money.

DSP-TN-21091

DSP-MO-20087

principal display panel

Sealed With Printed Neckband For Your Protection

IMPORTANT: READ DIRECTIONS FOR PROPER USE

Compare to Listerine Total Care Anticavity Mouthwash*

Anticavity

Fluoride

Rinse

ANTICAVITY FLUORIDE MOUTHWASH

EUCALYPTUS MINT

restores minerals to enamel

kills bad breath germs

helps prevent cavities

sugar free

1 L (1 QT 1.8 FL OZ) 33.8 FL OZ